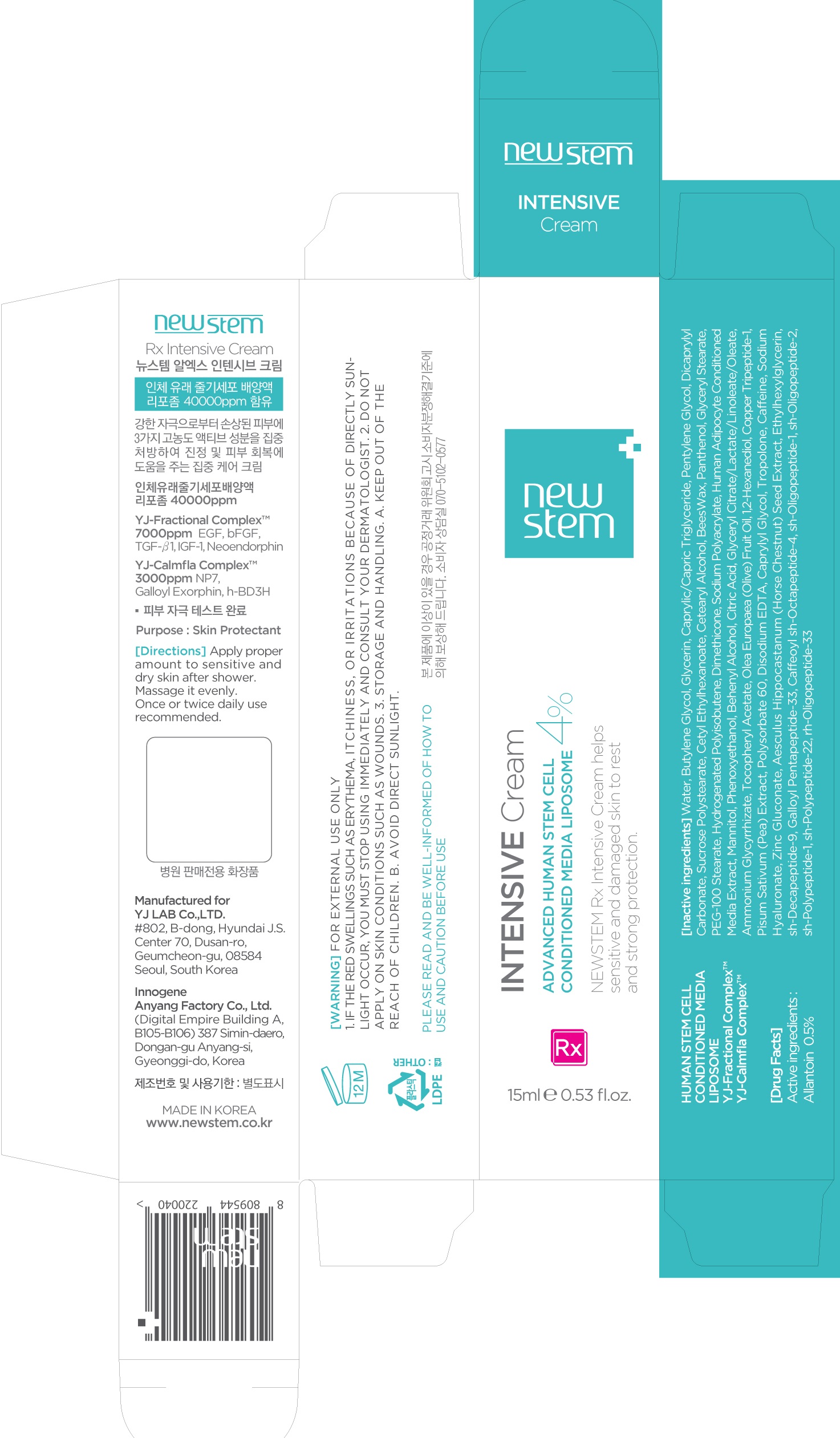 DRUG LABEL: NEWSTEM Rx Intensive
NDC: 71759-040 | Form: CREAM
Manufacturer: Yj Lab Co., Ltd.
Category: otc | Type: HUMAN OTC DRUG LABEL
Date: 20200410

ACTIVE INGREDIENTS: Allantoin 0.075 g/15 mL
INACTIVE INGREDIENTS: Water; Butylene Glycol

ACTIVE INGREDIENT

Active ingredients: Allantoin 0.5%

INACTIVE INGREDIENT

Inactive ingredients: Water, Butylene Glycol, Glycerin, Caprylic/Capric Triglyceride, Pentylene Glycol, Dicaprylyl Carbonate, Sucrose Polystearate, Cetyl Ethylhexanoate, Cetearyl Alcohol, BeesWax, Panthenol, Glyceryl Stearate, PEG-100 Stearate, Hydrogenated Polyisobutene, Dimethicone, Sodium Polyacrylate, Human Adipocyte Conditioned Media Extract, Mannitol, Phenoxyethanol, Behenyl Alcohol, Citric Acid, Glyceryl Citrate/Lactate/Linoleate/Oleate, Ammonium Glycyrrhizate, Tocopheryl Acetate, Olea Europaea (Olive) Fruit Oil, 1,2-Hexanediol, Copper Tripeptide-1, Pisum Sativum (Pea) Extract, Polysorbate 60, Disodium EDTA, Caprylyl Glycol, Tropolone, Caffeine, Sodium Hyaluronate, Zinc Gluconate, Aesculus Hippocastanum (Horse Chestnut) Seed Extract, Ethylhexylglycerin, sh-Decapeptide-9, Galloyl Pentapeptide-33, Caffeoyl sh-Octapeptide-4, sh-Oligopeptide-1, sh-Oligopeptide-2, sh-Polypeptide-1, sh-Polypeptide-22, rh-Oligopeptide-33

PURPOSE

Purpose: Skin Protectant

WARNINGS

Warnings: For external use only 1. If the Red swellings such as erythema, itchiness, or irritations because of directly sunlight occur, you must stop using immediately and Consult your dermatologist. 2. Do not apply on skin conditions such as wounds. 3. Storage and Handling. a. Keep out of the reach of children. b. Avoid direct sunlight.

KEEP OUT OF REACH OF CHILDREN

Uses

Uses: NEWSTEM Rx Intensive Cream helps sensitive and damaged skin to rest and strong protection.

Directions

Directions: Apply proper amount to sensitive and dry skin after shower. Massage it evenly. Once or twice daily use recommended.